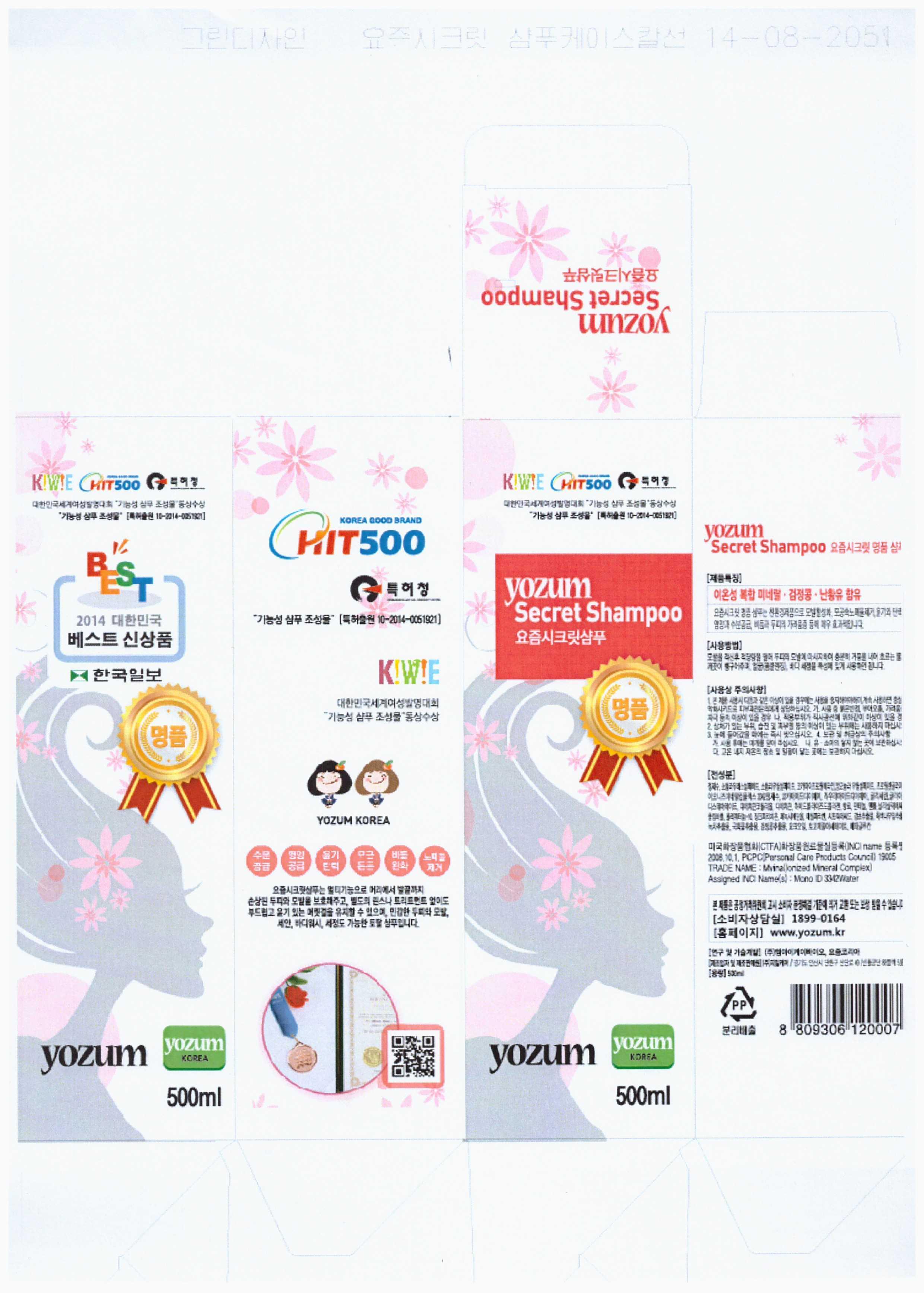 DRUG LABEL: YOZUM SECRET
NDC: 69525-1001 | Form: SHAMPOO
Manufacturer: YOZUM KOREA 
Category: otc | Type: HUMAN OTC DRUG LABEL
Date: 20150111

ACTIVE INGREDIENTS: GLYCERIN 2.5 g/100 mL
INACTIVE INGREDIENTS: WATER; DIMETHICONE; PANTHENOL

Drug Facts

ACTIVE INGREDIENT

glycerin

INACTIVE INGREDIENT

water, sodium lauryl sulfate, propylene glycol, dimethicone, panthenol, menthol etc

PURPOSE

scalp protectant

keep out of reach of the children

INDICATIONS AND USAGE

after soaking the hair in it, take a proper amount of it and then massage scalp and hair

WARNINGS

keep in a cool place do not store in high temperature condition

DOSAGE AND ADMINISTRATION

for external use only